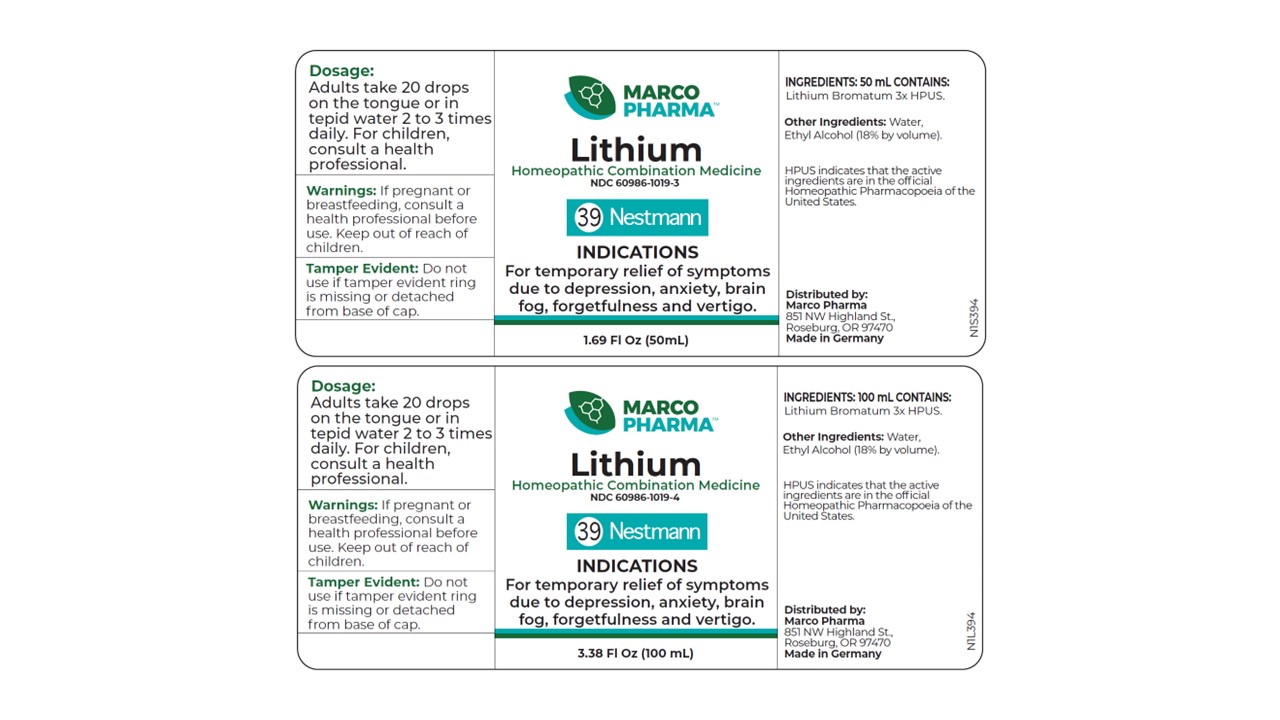 DRUG LABEL: Lithium
NDC: 60986-1019 | Form: LIQUID
Manufacturer: Marco Pharma International LLC.
Category: homeopathic | Type: HUMAN OTC DRUG LABEL
Date: 20260112

ACTIVE INGREDIENTS: LITHIUM BROMIDE 3 [hp_X]/1 mL
INACTIVE INGREDIENTS: WATER; ALCOHOL

Drug Facts

Active Ingredients

Lithium Bromatum 3xHPUS

The letters HPUS indicates that the components in this product are officially monographed in the Homeopathic Pharmacopoeia of United Sates.

Purpose

For the temporary relief of symptoms due to depression, anxiety, and vertigo.

Keep out of reach of children.

Dosage

Adults: Take 20 drops on the toungue or in water two to three times daily. Children receive 1/2 of the adult amount.

Warnings

If pregnant or breast-feeding, consult a health professional before use.

DOSAGE AND ADMINISTRATION

(Read Suggested Use Section)

Inactive Ingredients

Ethyl alcohol (18% by vol.) and water.